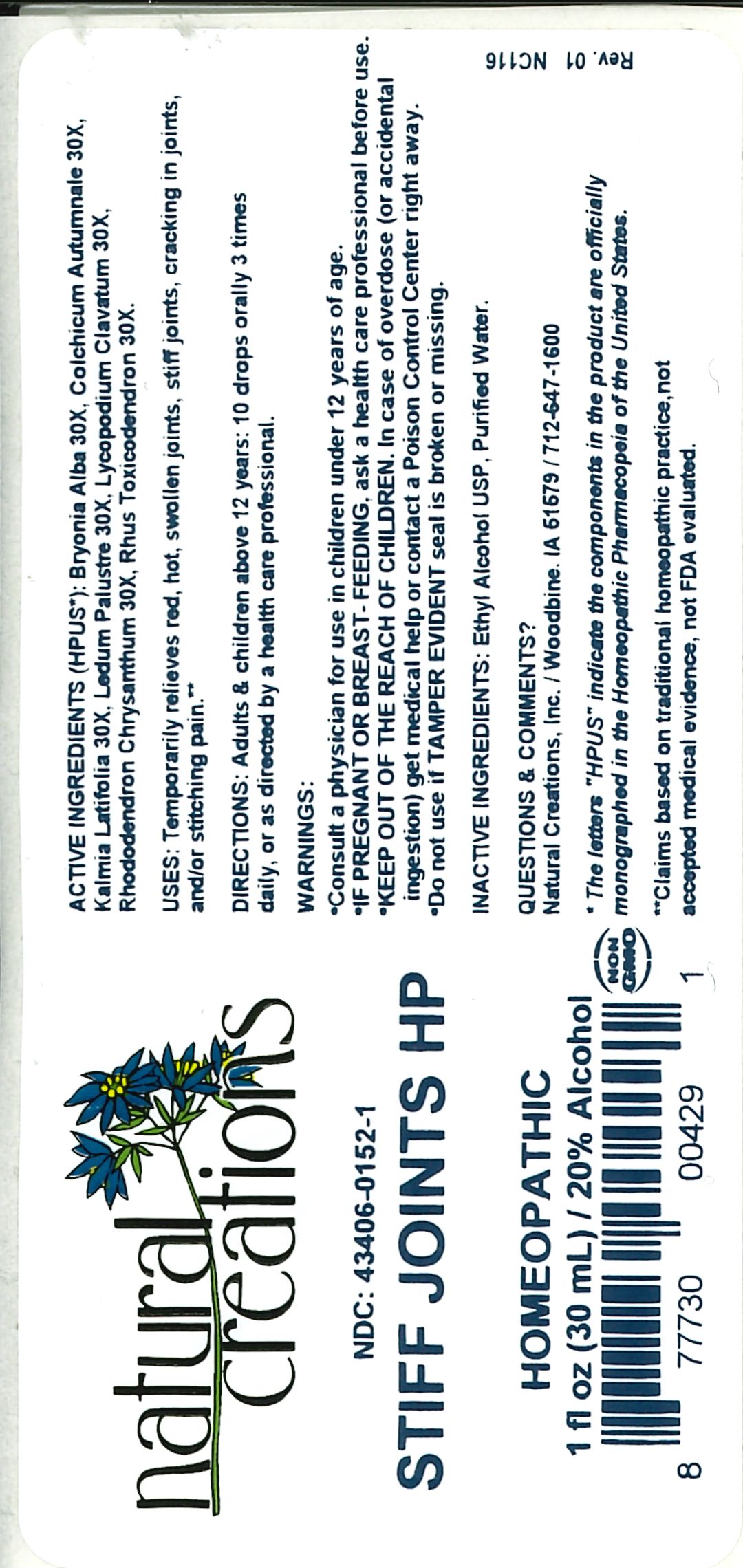 DRUG LABEL: STIFF JOINTS HP
NDC: 43406-0152 | Form: LIQUID
Manufacturer: Natural Creations, Inc.
Category: homeopathic | Type: HUMAN PRESCRIPTION DRUG LABEL
Date: 20230109

ACTIVE INGREDIENTS: BRYONIA ALBA ROOT 30 [hp_X]/1 mL; COLCHICUM AUTUMNALE BULB 30 [hp_X]/1 mL; KALMIA LATIFOLIA LEAF 30 [hp_X]/1 mL; LEDUM PALUSTRE TWIG 30 [hp_X]/1 mL; LYCOPODIUM CLAVATUM SPORE 30 [hp_X]/1 mL; RHODODENDRON AUREUM LEAF 30 [hp_X]/1 mL; TOXICODENDRON PUBESCENS LEAF 30 [hp_X]/1 mL
INACTIVE INGREDIENTS: WATER; ALCOHOL

STIFF JOINTS HP

ACTIVE INGREDIENT

ACTIVE INGREDIENTS (HPUS*): Bryonia Alba 30X, Colchicum Autumnale 30X, Kalmia Latifolia 30X, Ledum Palustre 30X, Lycopodium Clavatum 30X, Rhododendron Chrysanthum 30X, Rhus Toxicodendron 30X

INDICATIONS AND USAGE

USES: Temporarily relieves red, hot, swollen joints, stiff joints, cracking in joints, &/or stitching pain.**

WARNING:

- Consult a physician for use in children under 12 years of age.
- IF PREGNANT OR BREAST-FEEDING, ask a health care professional before use.
- KEEP OUT OF THE REACH OF CHILDREN. In case of overdose (or accidental ingestion) get medical help or contact a Poison Control Center right away.
- Do not use if TAMPER EVIDENT seal is broken or missing.

DOSAGE AND ADMINISTRATION

DIRECTIONS: Adults and children above 12 years: 10 drops orally 3 times daily, or as directed by a health care professional.

REFERENCES

*The letters "HPUS" indicate the components in the product are officially monographed in the Homeopathic Pharmacopeia of the United States.

**Claims based on traditional homeopathic practice, not accepted medical evidence. Not FDA evaluated.

INACTIVE INGREDIENTS: Purified Water, USP Ethanol Alcohol 20%

QUESTIONS AND COMMENTS?

Natural Creations / Woodbine, IA 51579 / 712-647-1600

PURPOSE

USES: Temporarily relieves red, hot swollen joints, stiff joints, cracking in joints, &/or stitching pain.**

KEEP OUT OF REACH OF CHILDREN

KEEP OUT OF THE REACH OF CHILDREN. In case of overdose (or accidental ingestion) get medical help or contact a Poison Control Center.

PACKAGE LABEL

NDC: 43406-0152-1

STIFF JOINTS HP

HOMEOPATHIC

1 fl oz (30 mL) / 20% Alcohol